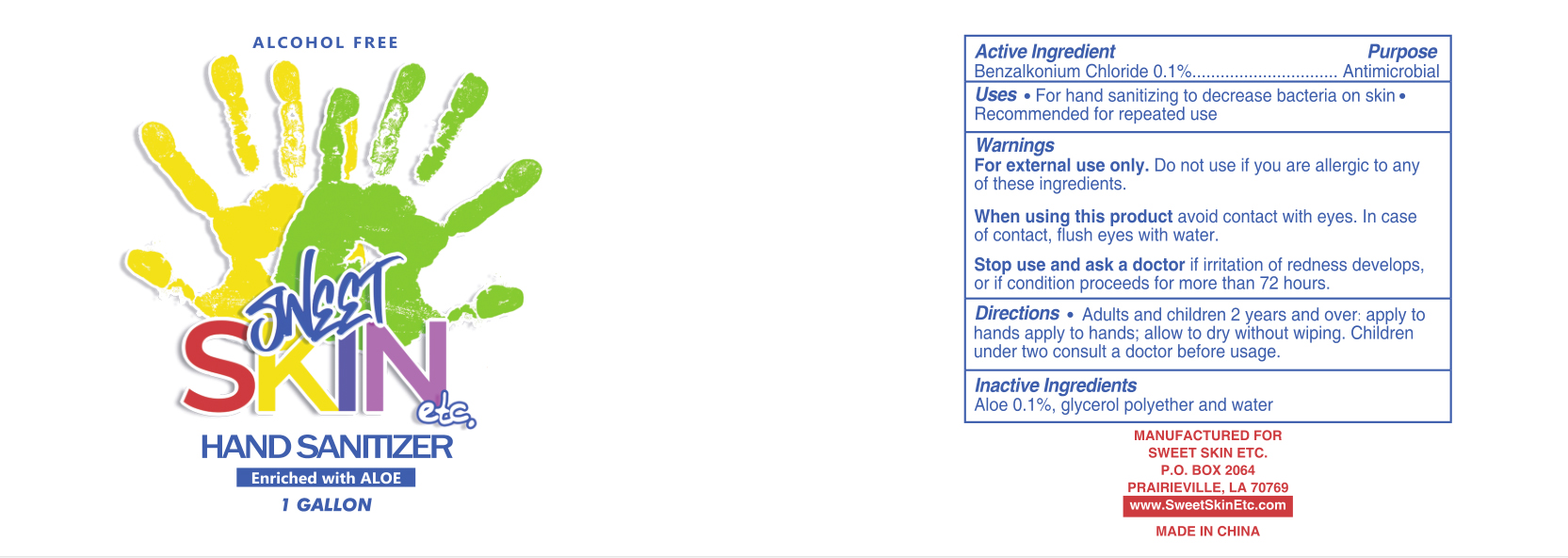 DRUG LABEL: Sweet skin Hand sanitizer
NDC: 80958-001 | Form: GEL
Manufacturer: Sweet Skin Etc. Llc
Category: otc | Type: HUMAN OTC DRUG LABEL
Date: 20230213

ACTIVE INGREDIENTS: BENZALKONIUM CHLORIDE 1 g/1 L
INACTIVE INGREDIENTS: ALOE; WATER; GLYCERIN

Sweet skin Hand sanitizer

Active Ingredient

Benzalkonium Chloride 0.1% Antimicrobial

Purpose

Antimicrobial

Uses

- For hand sanitizing to decrease bacteria on skin
- Recommended for repeated use

Warnings

For external use only. Do not use if you are allergic to any of these ingredients

When using this product

avoid contact with eyes. In case of contact, flush eyes with water.

Stop use and ask a doctor

if irritation of redness develops, or if condition proceeds for more than 72 hours.

Children under two consult a doctor before usage.

Directions

Adults and children 2 years and over: apply to hands; allow to dry without wiping.

Children under two consult a doctor before usage.

Inactive Ingredients

Aloe 0.1%, glycerol polyether and water

Package Label - Principal Display Panel

3.785 L NDC: 80958-019-01

ALCOHOL FREE

SWEET

SKIN etc.

HAND SANITIZER

Enriched with ALOE

1 GALLON